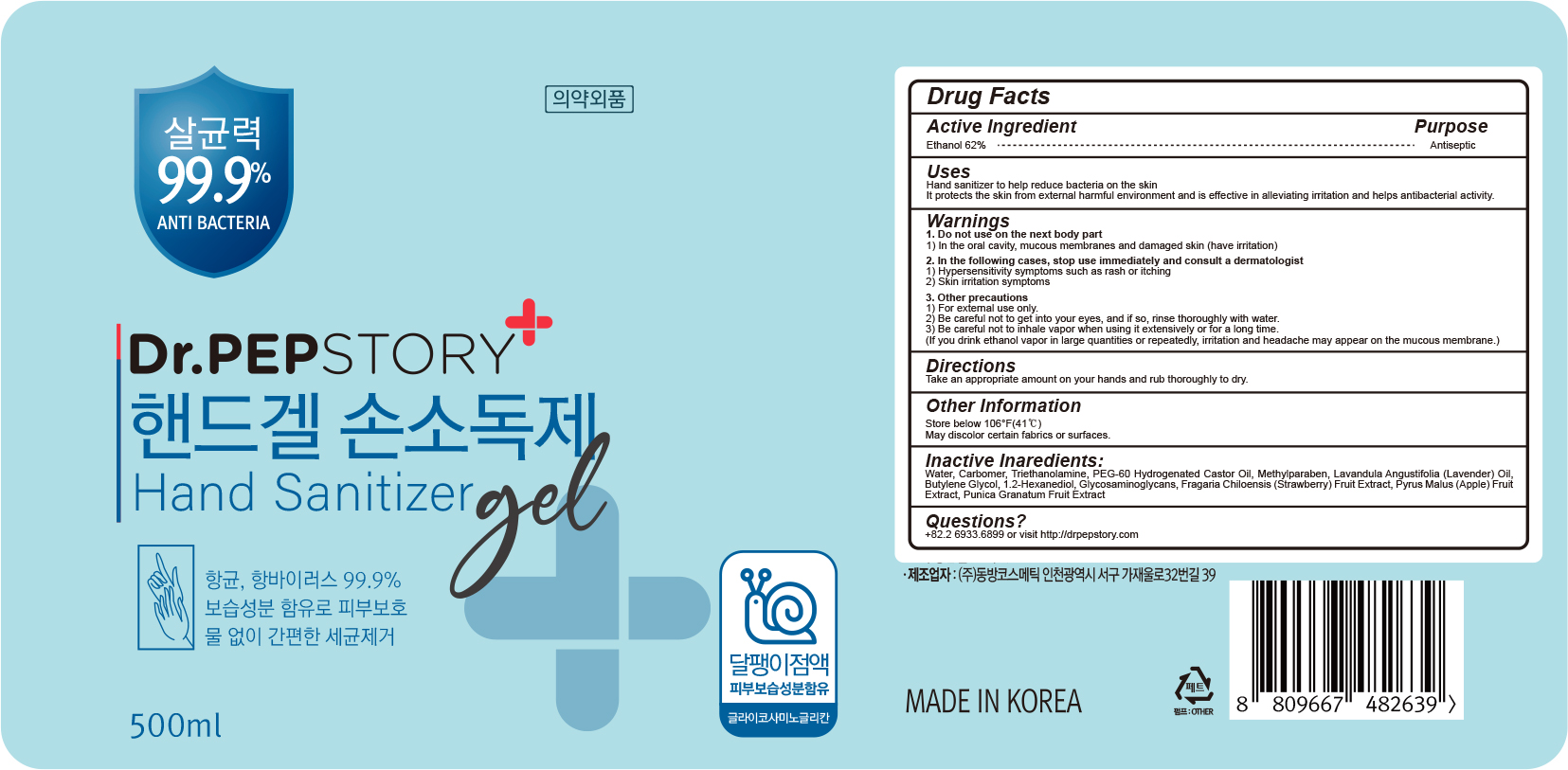 DRUG LABEL: Dr PEPSTORY HAND SANITIZER
NDC: 74354-010 | Form: GEL
Manufacturer: Kiposs Co.,ltd
Category: otc | Type: HUMAN OTC DRUG LABEL
Date: 20200406

ACTIVE INGREDIENTS: ALCOHOL 62 g/100 mL
INACTIVE INGREDIENTS: Water; CARBOMER HOMOPOLYMER, UNSPECIFIED TYPE; TROLAMINE; PEG-60 Hydrogenated Castor Oil; Methylparaben; LAVENDER OIL; Butylene Glycol; 1,2-HEXANEDIOL; POLYSULFATED GLYCOSAMINOGLYCAN; BEACH STRAWBERRY; APPLE; POMEGRANATE

ACTIVE INGREDIENT

Active ingredients: ALCOHOL 62%

INACTIVE INGREDIENT

Inactive ingredients:
Water, Carbomer, Triethanolamine, PEG-60 Hydrogenated Castor Oil, Methylparaben, Lavandula Angustifolia (Lavender) Oil, Butylene Glycol,
1.2-Hexanediol, Glycosaminoglycans, Fragaria Chiloensis (Strawberry) Fruit Extract, Pyrus Malus (Apple) Fruit Extract, Punica Granatum Fruit Extract

PURPOSE

Purpose: Antiseptic

WARNINGS

1. Do not use on the next body part
1) In the oral cavity, mucous membranes and damaged skin (have irritation)
2. In the following cases, stop use immediately and consult a dermatologist
1) Hypersensitivity symptoms such as rash or itching
2) Skin irritation symptoms
3. Other precautions
1) For external use only.
2) Be careful not to get into your eyes, and if so, rinse thoroughly with water.
3) Be careful not to inhale vapor when using it extensively or for a long time.
(If you drink ethanol vapor in large quantities or repeatedly, irritation and headache may appear
on the mucous membrane.)

KEEP OUT OF REACH OF CHILDREN

Uses

Hand sanitizer to help reduce bacteria on the skin
It protects the skin from external harmful environment and is effective in alleviating irritation and helps antibacterial activity.

Directions

Take an appropriate amount on your hands and rub thoroughly to dry.

Other Information

Store below 106F(41C)
May discover certain fabrics or surfaces.

Questions

+82.2.6933.6899 or visit http://drpepstory.com